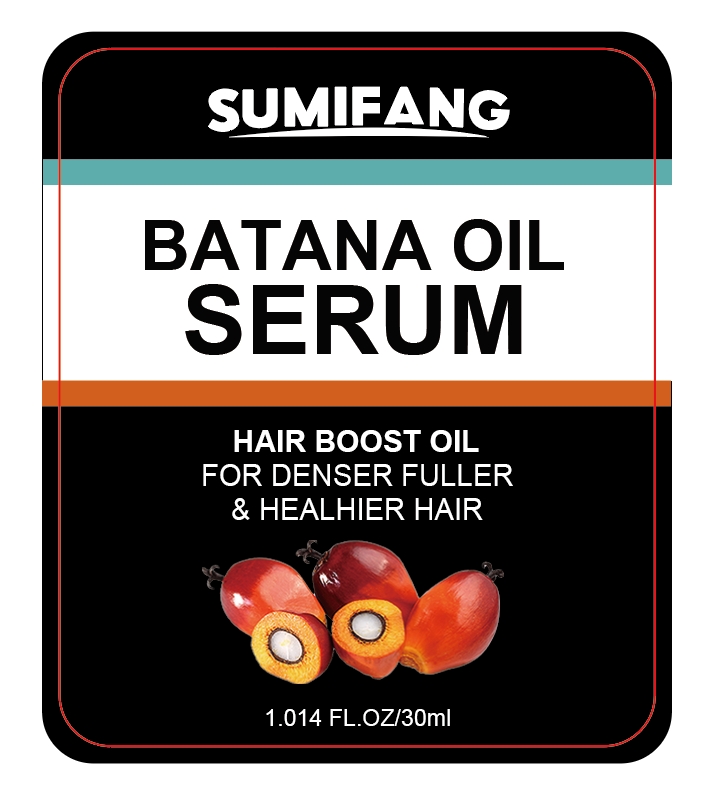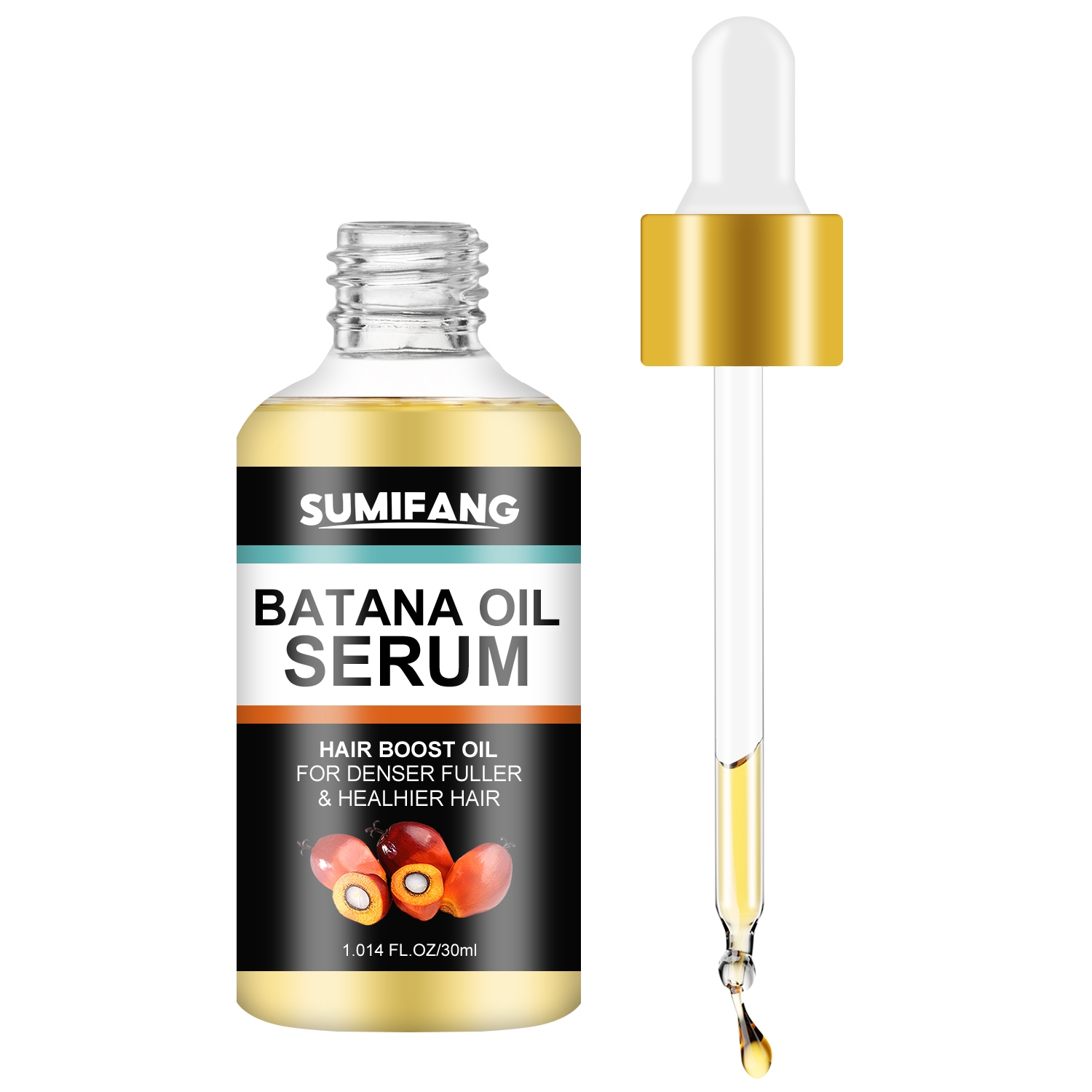 DRUG LABEL: Batana OilSerum
NDC: 84025-235 | Form: OIL
Manufacturer: Guangzhou Yanxi Biotechnology Co., Ltd
Category: otc | Type: HUMAN OTC DRUG LABEL
Date: 20241025

ACTIVE INGREDIENTS: 1,2-BUTANEDIOL 3 mg/100 mL; RICINUS COMMUNIS (CASTOR) SEED OIL 5 mg/100 mL
INACTIVE INGREDIENTS: WATER

DOSAGE AND ADMINISTRATION

use as normal hair oil

WARNINGS

Keep out of children

INACTIVE INGREDIENT

AQUA

INDICATIONS AND USAGE

for daily hair care

keep out of children

PURPOSE

strong and nourishing hair